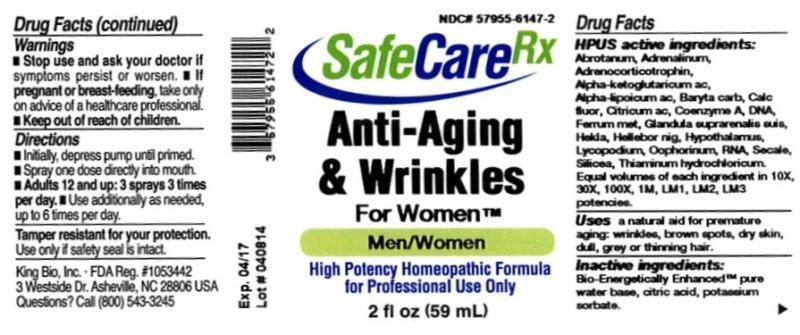 DRUG LABEL: Anti-Aging and Wrinkles For Women
NDC: 57955-6147 | Form: LIQUID
Manufacturer: King Bio Inc.
Category: homeopathic | Type: HUMAN OTC DRUG LABEL
Date: 20140421

ACTIVE INGREDIENTS: ARTEMISIA ABROTANUM FLOWERING TOP 10 [hp_X]/59 mL; EPINEPHRINE 10 [hp_X]/59 mL; CORTICOTROPIN 10 [hp_X]/59 mL; .ALPHA.-KETOGLUTARIC ACID 10 [hp_X]/59 mL; .ALPHA.-LIPOIC ACID 10 [hp_X]/59 mL; BARIUM CARBONATE 10 [hp_X]/59 mL; CALCIUM FLUORIDE 10 [hp_X]/59 mL; ANHYDROUS CITRIC ACID 10 [hp_X]/59 mL; COENZYME A 10 [hp_X]/59 mL; HERRING SPERM DNA 10 [hp_X]/59 mL; IRON 10 [hp_X]/59 mL; SUS SCROFA ADRENAL GLAND 10 [hp_X]/59 mL; HEKLA LAVA 10 [hp_X]/59 mL; HELLEBORUS NIGER ROOT 10 [hp_X]/59 mL; BOS TAURUS HYPOTHALAMUS 10 [hp_X]/59 mL; LYCOPODIUM CLAVATUM SPORE 10 [hp_X]/59 mL; SUS SCROFA OVARY 10 [hp_X]/59 mL; SACCHAROMYCES CEREVISIAE RNA 10 [hp_X]/59 mL; CLAVICEPS PURPUREA SCLEROTIUM 10 [hp_X]/59 mL; SILICON DIOXIDE 10 [hp_X]/59 mL; THIAMINE HYDROCHLORIDE 10 [hp_X]/59 mL
INACTIVE INGREDIENTS: WATER; CITRIC ACID MONOHYDRATE; POTASSIUM SORBATE

Anti-Aging and Wrinkles For Women™

ACTIVE INGREDIENT

Drug Facts__________________________________________________________________________________________________________

HPUS active ingredients: Abrotanum, Adrenalinum, Adrenocorticotrophin, Alpha-Ketoglutaricum acidum, Alpha-lipoicum acidum, Baryta carbonica, Calcarea fluorica, Citricum acidum, Coenzyme A, DNA, Ferrum metallicum, Glandula suprarenalis suis, Hekla lava, Helleborus niger, Hypothalamus, Lycopodium clavatum, oophorinum, RNA, Secale cornutum, Silicea, Thiaminum hydrochloricum. Equal volumes of each ingredient in 10X, 30X, 100X, 1M, LM1, LM2, LM3 potencies.

INDICATIONS AND USAGE

Uses a natural aid for premature aging: wrinkles, brown spots, dry skin, dull, grey or thinning hair.

Inactive Ingredients:

Bio-Energetically Enhanced™ pure water, citric acid and potassium sorbate.

Warnings

- Stop use and ask your doctor if symptoms persist or worsen.
- If pregnant or breast-feeding, take only on advice of a healthcare professional.

- Keep out of reach of children.

Directions

- Initially, depress pump until primed.
- Spray one dose directly into mouth.
- Adults 12 and up: 3 sprays 3 times per day.
- Use additionally as needed, up to 6 times per day.

OTHER SAFETY INFORMATION

Tamper resistant for your protection. Use only if safety seal is intact.

PURPOSE

Uses a natural aid for premature aging:

- wrinkles
- brown spots
- dry skin
- dull, grey or thinning hair